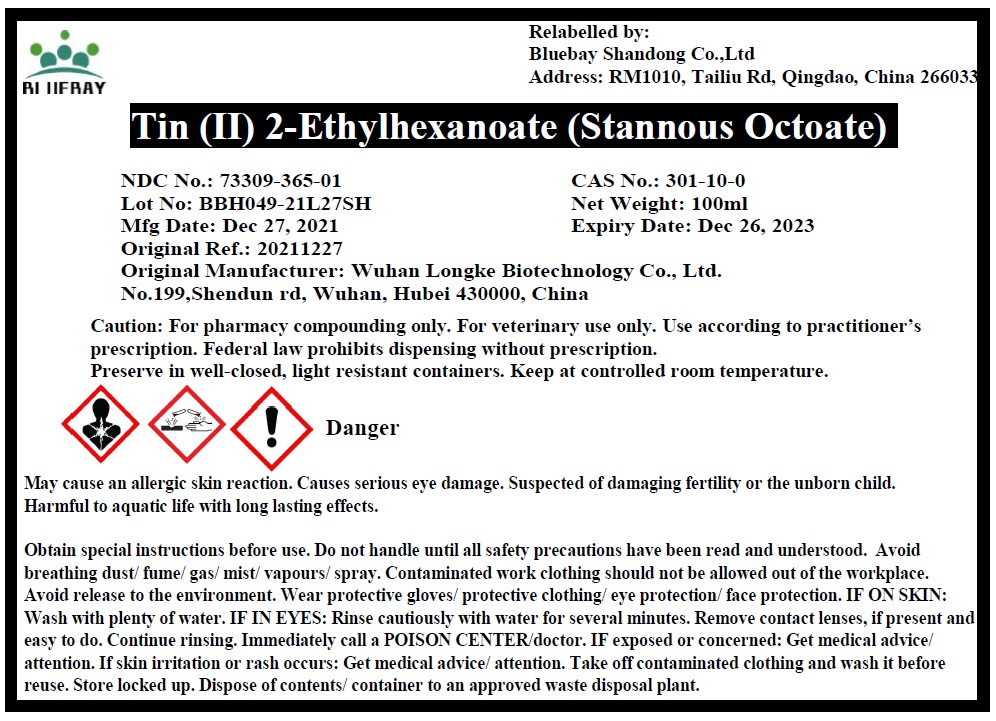 DRUG LABEL: Tin (II) 2-Ethylhexanoate (Stannous octoate)
NDC: 73309-365 | Form: LIQUID
Manufacturer: BLUEBAY SHANDONG CO.,LTD
Category: other | Type: BULK INGREDIENT - ANIMAL DRUG
Date: 20220225

ACTIVE INGREDIENTS: STANNOUS 2-ETHYLHEXANOATE 1 g/1 g

Tin (II) 2-Ethylhexanoate (Stannous octoate)